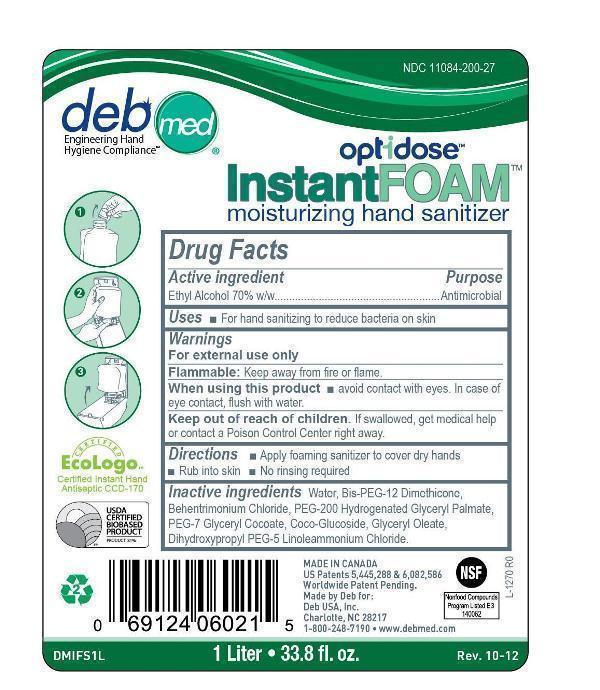 DRUG LABEL: Deb Med InstantFOAM OptiDose Hand Sanitizer
NDC: 11084-200 | Form: LIQUID
Manufacturer: Deb USA, Inc.
Category: otc | Type: HUMAN OTC DRUG LABEL
Date: 20121030

ACTIVE INGREDIENTS: ALCOHOL 70 mL/100 mL
INACTIVE INGREDIENTS: WATER 1 mL/100 mL; DIHYDROXYPROPYL PEG-5 LINOLEAMMONIUM CHLORIDE 1 mL/100 mL; PROPYL ALCOHOL 1 mL/100 mL; BEHENTRIMONIUM CHLORIDE 1 mL/100 mL; DIMETHICONE 1 mL/100 mL; COCO GLUCOSIDE 1 mL/100 mL; GLYCERYL MONOOLEATE 1 mL/100 mL; PEG-200 DILAURATE 1 mL/100 mL; GLYCERYL COCOATE 1 mL/100 mL

Drug Facts

Active ingredient

Ethyl Alcohol 70% w/w

Purpose

Antimicrobial

Uses

For hand sanitizing to reduce bacteria on skin

Warnings

For external use only

Flammable: Keep away from fire or flame.

When using this product

Keep out of reach of children.

If swallowed, get medical help or contact a Poison Control Center right away.

Directions

Apply foaming sanitizer to cover dry hands

Rub into skin

No rinsing required

Inactive ingredients

Water, Bis-PEG-12 Dimethicone, Behentrimonium Chloride, PEG-200 Hydrogenated Glyceryl Palmate, PEG-7 Glyceryl Cocoate, Coco-Glucoside, Glyceryl Oleate, Dihydroxypropyl PEG-5 Linoleammonium Chloride.

PACKAGE LABEL

deb med

Engineering Hand Hygiene Compliance

NDC 11084-200-27

optidose

InstantFOAM moisturing hand sanitizer

Certified EcoLogo

Certified Instant Hand Antiseptic CCD-170

USDA Certified Biobased Product

Made in Canada

US Patents 5,445,288 & 6,082,586

Worldwide Patent Pending.

Made by Deb for:

Deb USA, Inc.

Charlotte, NC 28217

1-800-248-7190

www.debmed.com

NSF

Nonfood Compounds Program Listed E3

140062

DMIFS1L

1 Liter 33.8 fl. oz.

Rev. 10-12